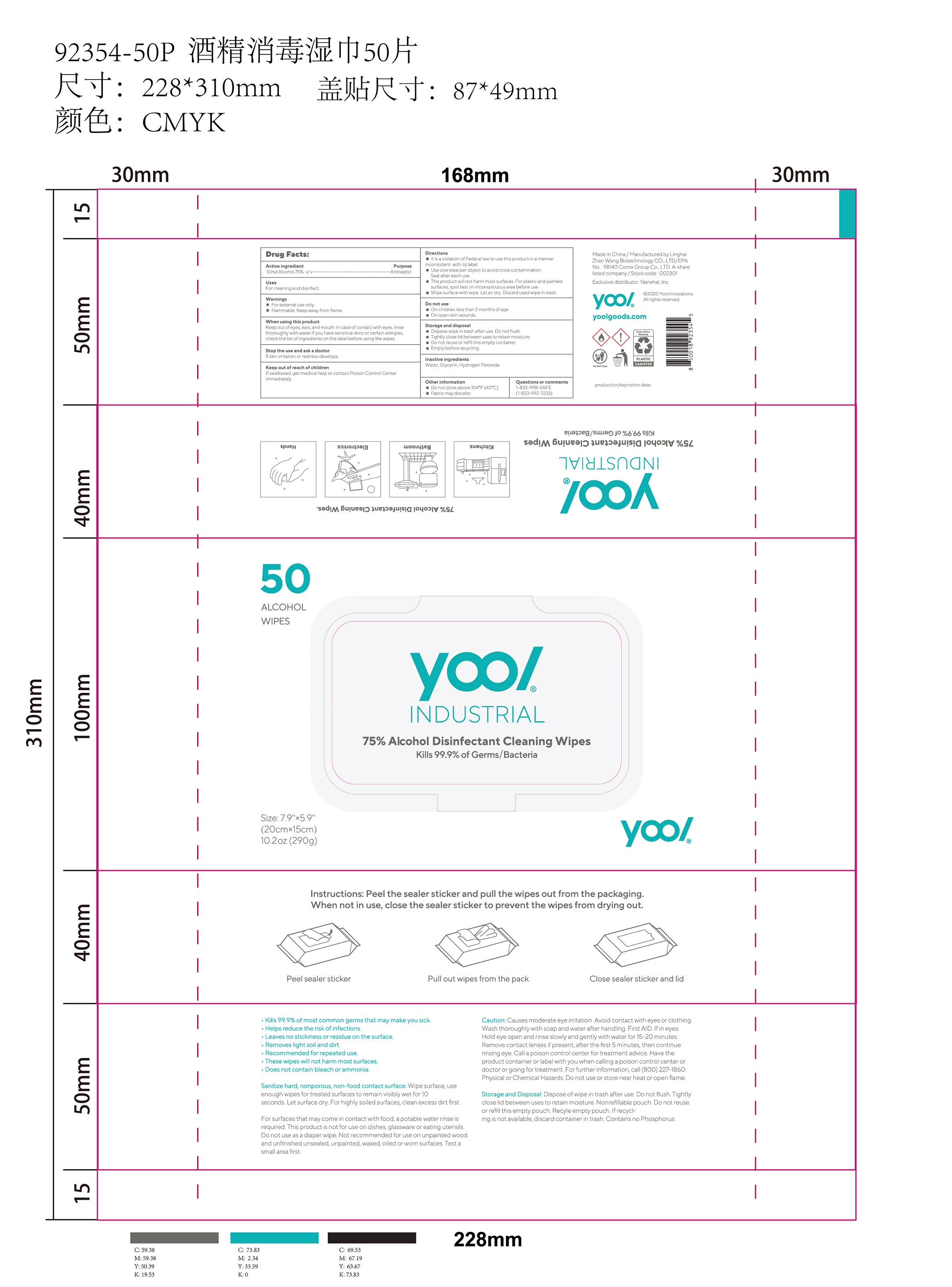 DRUG LABEL: 75% Alcohol Disinfectant Cleaning Wipes
NDC: 75269-006 | Form: CLOTH
Manufacturer: LINGHAI ZHANWANG BIOTECHNOLOGY CO.,LTD.
Category: otc | Type: HUMAN OTC DRUG LABEL
Date: 20231024

ACTIVE INGREDIENTS: ALCOHOL 75 mL/100 mL
INACTIVE INGREDIENTS: GLYCERIN; WATER; HYDROGEN PEROXIDE

75269-006 75% Alcohol Disinfectant Cleaning Wipes

Active ingredient

Ethyl Alcohol 75% v/ v

Purpose

Antiseptic

Uses

For cleaning and disinfect.

Warnings

For external use only.

Flammable. Keep away from flame.

When using this product

Keep out of eyes, ears, and mouth. In case of contact with eyes, rinse thoroughly with water.lf you have sensitive skins or certain allergies, check the list of ingredients on the label before using the wipes.

STOP USE

Stop the use and ask a doctor If skin irritation or redness develops.

Keep out of reach of children

If swallowed, get medical help or contact Poison Control Center immediately.

Directions

It is a violation of Federal law to use this product in a manner inconsistent with its label.

Use one wipe per object to avoid cross contamination.

Seal after each use.

This product will not harm most surfaces. For plastic and painted surfaces, spot test on inconspicuous area before use.

Wipe surface with wipe. Let air dry. Discard used wipe in trash.

Do not use

On children less than 2 months of age.

On open skin wounds.

Storage and disposal

Dispose wipe in trash after use. Do not flush.

Tightly close lid between uses to retain moisture.

Do not reuse or refill this empty container.

Empty before recycling.

Inactive ingredients

Water, Glycerin, Hydrogen Peroxide

Other information

Do not store above 104®F (40°C).

Fabric may discolor.

PACKAGE LABEL

50 ALCOHOL WIPES; NDC: 75269-006-01